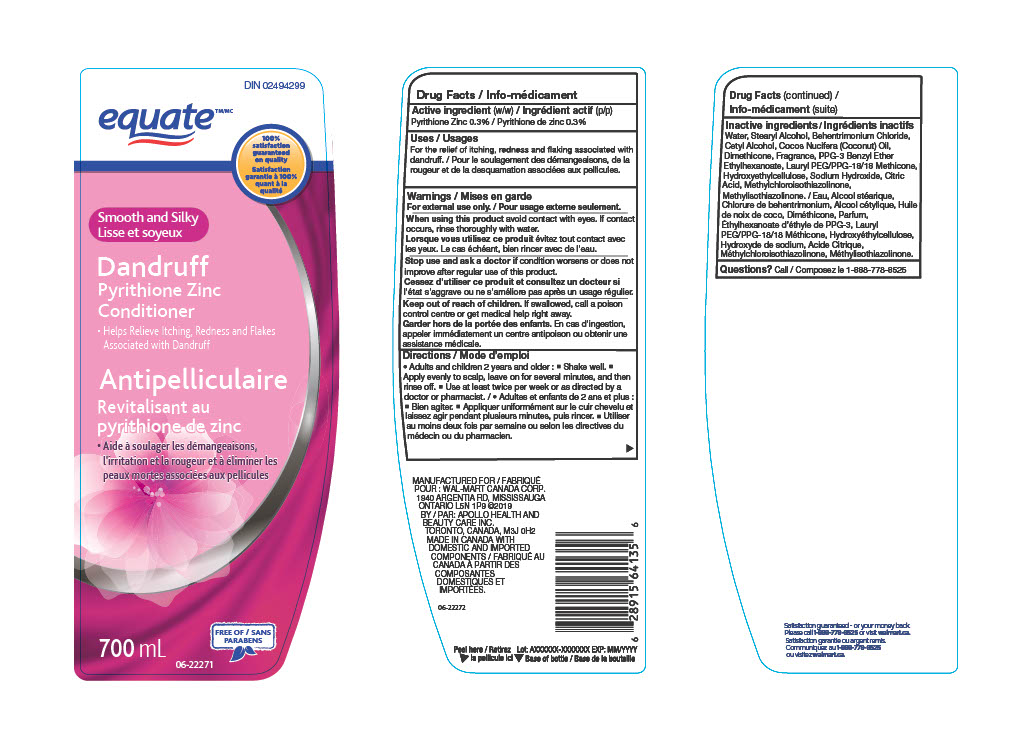 DRUG LABEL: Equate
NDC: 79903-900 | Form: SHAMPOO
Manufacturer: Wal-Mart Stores, Inc
Category: otc | Type: HUMAN OTC DRUG LABEL
Date: 20241019

ACTIVE INGREDIENTS: PYRITHIONE ZINC 300 mg/100 mL
INACTIVE INGREDIENTS: WATER; STEARYL ALCOHOL; COCONUT OIL; LAURYL PEG/PPG-18/18 METHICONE; SODIUM HYDROXIDE; ANHYDROUS CITRIC ACID; CETYL HYDROXYETHYLCELLULOSE (350000 MW); METHYLCHLOROISOTHIAZOLINONE; BEHENTRIMONIUM CHLORIDE; DIMETHICONE; FRAGRANCE CLEAN ORC0600327; PPG-3 BENZYL ETHER ETHYLHEXANOATE; METHYLISOTHIAZOLINONE; CETYL ALCOHOL

Equate shampoo-smooth and silky, NDC 79903-900

ACTIVE INGREDIENT

Pyrithione Zinc

PURPOSE

For the relief of itching, redness and flaking associated with dandruff

WARNINGS

For External use

WHEN USING

Stop contact with eyes. If contact occurs, rinse eyes thoroughly with water.

Stop use and ask a doctor if condition worsens or does not improve after regular use of the product.

KEEP OUT OF REACH OF CHILDREN

If swallowed, call a poison control centre or get medical help right away.

DOSAGE AND ADMINISTRATION

Adults and children 2 years and older. Shake well. Apply evenly to scalp. leave on for several mimnutes and then rinse off. Use at least twice per week or as directed by a doctor or pharmacist.

STORAGE AND HANDLING

Store at room temperature

INACTIVE INGREDIENT

Water, Stearyl Alcohol, Behentrimonium Chloride, Cetyl Alcohol, Cocos Nucifera (Coconut) Oil, Dimethicone, Fragrance, PPG-3 Benzyl Ether Ethylhexanoate, Lauryl PEG/PPG-18/18 Methicone, Hydroxyethylcellulose, Sodium Hydroxide, Citric Acid, Methylchloroisothiazolinone, Methylisothiazolinone

INDICATIONS AND USAGE

Relieves itching , redness and flakes associated with Dandruff.